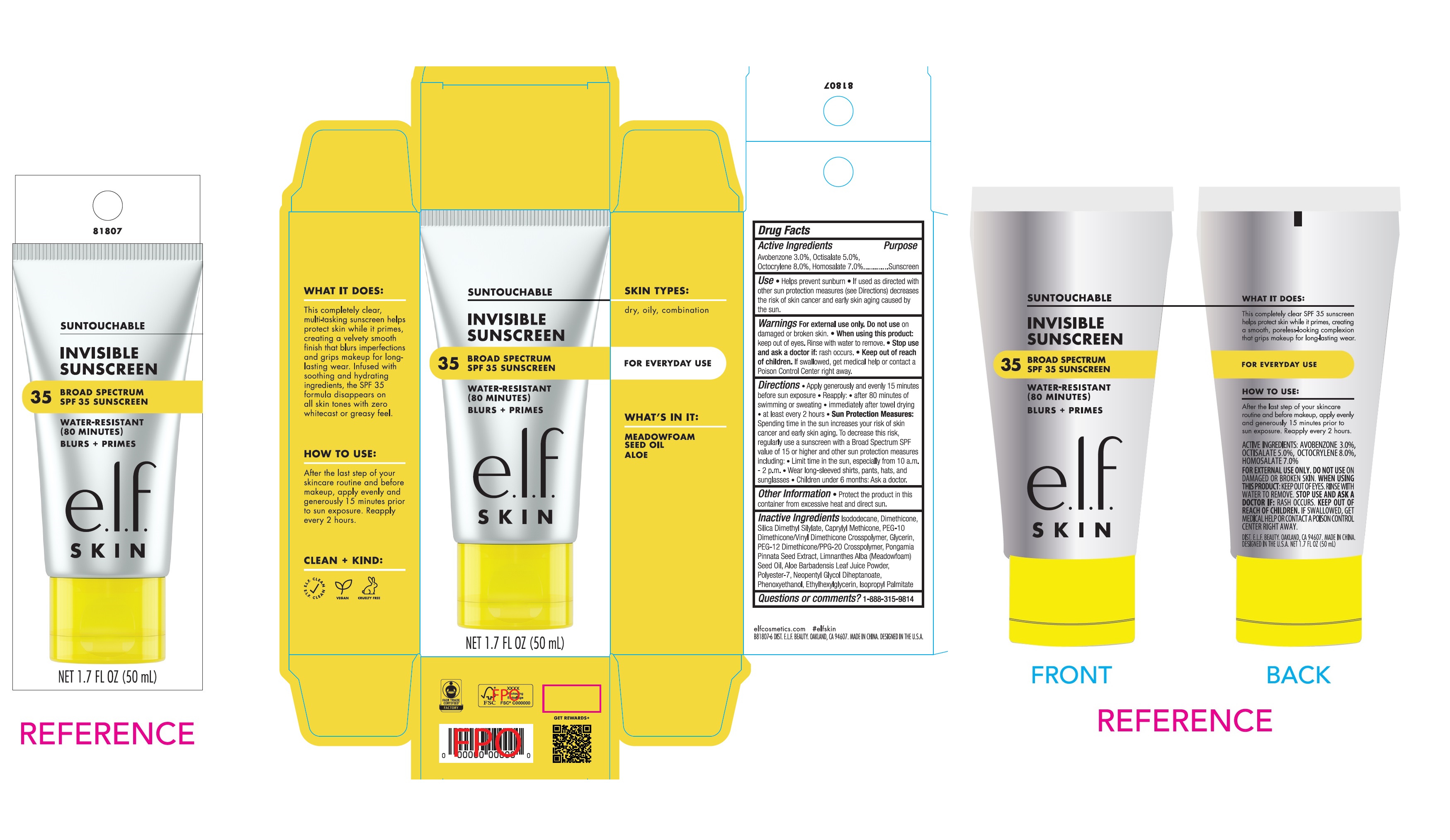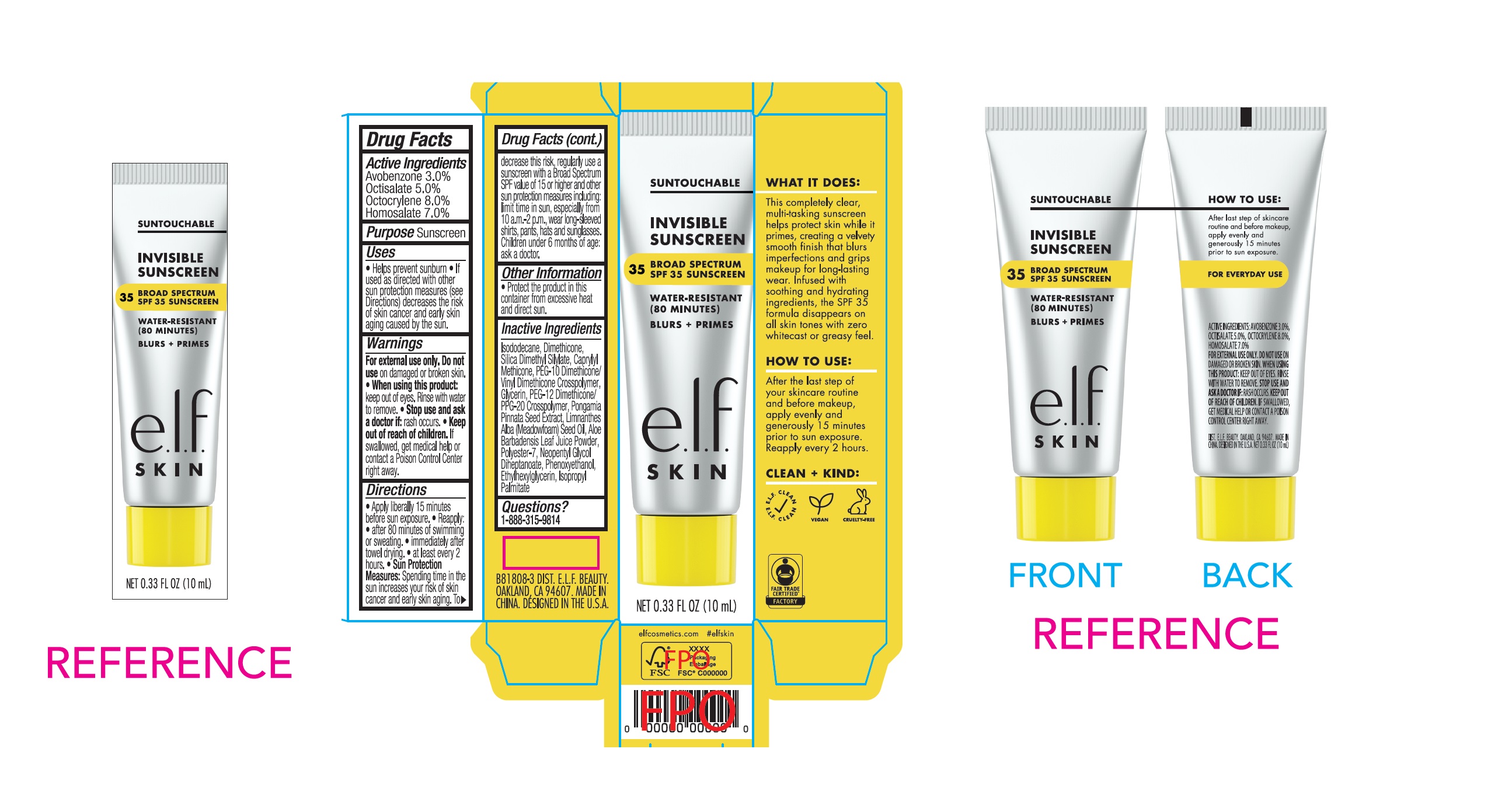 DRUG LABEL: e.l.f Invisible Sunscreen SPF 35
NDC: 76354-444 | Form: CREAM
Manufacturer: e.l.f. Cosmetics, Inc
Category: otc | Type: HUMAN OTC DRUG LABEL
Date: 20251107

ACTIVE INGREDIENTS: AVOBENZONE 30 mg/1 mL; OCTISALATE 50 mg/1 mL; OCTOCRYLENE 80 mg/1 mL; HOMOSALATE 70 mg/1 mL
INACTIVE INGREDIENTS: ISODODECANE; DIMETHICONE, UNSPECIFIED; SILICA DIMETHYL SILYLATE; CAPRYLYL TRISILOXANE; GLYCERIN; PEG-12 DIMETHICONE/PPG-20 CROSSPOLYMER; PONGAMIA PINNATA SEED; MEADOWFOAM SEED OIL; ALOE VERA LEAF; POLYESTER-7; NEOPENTYL GLYCOL DIHEPTANOATE; PHENOXYETHANOL; ETHYLHEXYLGLYCERIN; ISOPROPYL PALMITATE

e.l.f Invisible Sunscreen SPF 35

Active Ingredients

Avobenzone 3.0%

Octisalate 5.0%

Octocrylene 8.0%

Homosalate 7.0%

Purpose

Sunscreen

Use

- Helps prevent sunburn
- If used as directed with other sun protection measures (see Directions) decreases the risk of skin cancer and early skin aging caused by the sun.

Warnings

For external use only.

Do not use

on damaged or broken skin.

When using this product:

- keep out of eyes. Rinse with water to remove.

Stop use and ask a doctor if :

- rash occurs.

Keep out of reach of children.

- If swallowed, get medical help or contact a Poison Control Center right away.

Directions

- Apply generously and evenly 15 minutes before sun exposure.
- Reapply:
- after 80 minutes of swimming or sweating.
- immediately after towel drying.
- at least every 2 hours.
- Sun Protection Measures: Spending time in the sun increases your risk of skin cancer and early skin aging. To decrease this risk, regularly use a sunscreen with a Broad Spectrum SPF value of 15 or higher and other sun protection measures including:
- Limit time in sun, especially from 10 a.m.-2 p.m.
- Wear long-sleeved shirts, pants, hats and sunglasses.
- Children under 6 months: Ask a doctor.

Other Information

- Protect the product in this container from excessive heat and direct sun.

Inactive Ingredients

Isododecane, Dimethicone, Silica Dimethyl Silylate, Caprylyl Methicone, PEG-10 Dimethicone/Vinyl Dimethicone Crosspolymer, Glycerin, PEG-12 Dimethicone/PPG-20 Crosspolymer, Pongamia Pinnata Seed Extract, Limnanthes Alba (Meadowfoam) Seed Oil, Aloe Barbadensis Leaf Juice Powder, Polyester-7, Neopentyl Glycol Diheptanoate, Phenoxyethanol, Ethylhexylglycerin, Isopropyl Palmitate

Question or comments?

1-888-315-9814